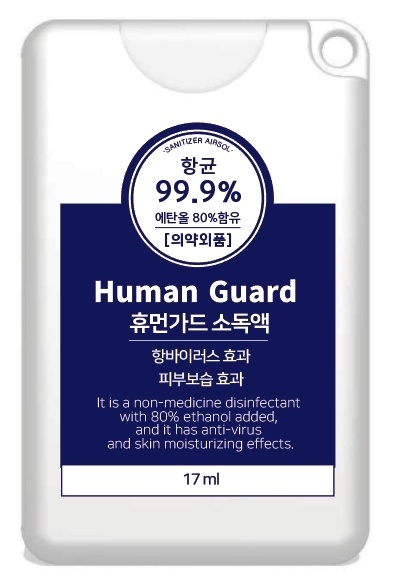 DRUG LABEL: Human Guard Sanitizer
NDC: 77637-500 | Form: AEROSOL, SPRAY
Manufacturer: DERMACOS KOREA
Category: otc | Type: HUMAN OTC DRUG LABEL
Date: 20210429

ACTIVE INGREDIENTS: ALCOHOL 80 mL/100 mL
INACTIVE INGREDIENTS: GLYCERIN; WATER; HYALURONATE SODIUM

Active Ingredient(s)

Alcohol 80% v/v. Purpose: Antimicrobial

Purpose

Antimicrobial, Hand Sanitizer

Use

To help reduce bacteria on the skin.

Warnings

For external use only. Flammable. Keep away from heat or flame

Do not use

- in children less than 2 months of age
- on open skin wounds

When using this product keep out of eyes, ears, and mouth. In case of contact with eyes, rinse eyes thoroughly with water.
Stop use and ask a doctor if irritation or rash occurs. These may be signs of a serious condition.
Keep out of reach of children. If swallowed, get medical help or contact a Poison Control Center right away.

Stop use and ask a doctor if irritation or rash occurs. These may be signs of a serious condition.

Keep out of reach of children. If swallowed, get medical help or contact a Poison Control Center right away.

Directions

- Open package and apply wipe throughly to hands.
- Allow to dry without wiping.
- Children under 6 years of age should be supervised when using this product.
- Not recommended for infants.

Other information

- Store at room temperature (33.8oF-86oF, 1oC-30oC) and avoid cold or dry place.
- May discolor certain fabrics or surfaces.
- Harmful to wood finishes and plastics.

Inactive ingredients

Fragrance (Lemon), Glycerin, Purified Water, Sodium Hyaluronate.